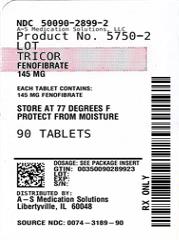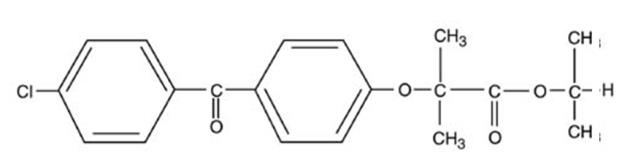 DRUG LABEL: Tricor
NDC: 50090-2899 | Form: TABLET
Manufacturer: A-S Medication Solutions
Category: prescription | Type: HUMAN PRESCRIPTION DRUG LABEL
Date: 20240429

ACTIVE INGREDIENTS: FENOFIBRATE 145 mg/1 1
INACTIVE INGREDIENTS: DOCUSATE SODIUM; SUCROSE; SODIUM LAURYL SULFATE; LACTOSE MONOHYDRATE; MAGNESIUM STEARATE; TITANIUM DIOXIDE; TALC; LECITHIN, SOYBEAN; XANTHAN GUM; POLYVINYL ALCOHOL, UNSPECIFIED; CROSPOVIDONE; MICROCRYSTALLINE CELLULOSE

HIGHLIGHTS OF PRESCRIBING INFORMATION

These highlights do not include all the information needed to use TRICOR safely and effectively. See full prescribing information for TRICOR.
TRICOR (fenofibrate) Tablet, for oral use
Initial U.S. Approval: 1993

RECENT MAJOR CHANGES

Warnings and Precautions, Hepatotoxicity (5.2) | 6/2021

1 INDICATIONS AND USAGE

TRICOR is a peroxisome proliferator-activated receptor (PPAR) alpha agonist indicated as an adjunct to diet:

- To reduce elevated LDL-C, Total-C, TG and Apo B, and to increase HDL-C in adult patients with primary hypercholesterolemia or mixed dyslipidemia (1.1).
- For treatment of adult patients with severe hypertriglyceridemia (1.2).

Limitations of Use: Fenofibrate was not shown to reduce coronary heart disease morbidity and mortality in patients with type 2 diabetes mellitus (5.1).

2 DOSAGE AND ADMINISTRATION

- Primary hypercholesterolemia or mixed dyslipidemia: Initial dose of 145 mg once daily (2.2).
- Severe hypertriglyceridemia: Initial dose of 48 to 145 mg once daily. Maximum dose is 145 mg (2.3).
- Renally impaired patients: Initial dose of 48 mg once daily (2.4).
- Geriatric patients: Select the dose on the basis of renal function (2.5).
- Maybe taken without regard to meals (2.1).

3 DOSAGE FORMS AND STRENGTHS

Oral Tablets: 48 mg and 145 mg (3).

4 CONTRAINDICATIONS

- Severe renal dysfunction, including dialysis patients (4, 8.6, 12.3).
- Active liver disease (4, 5.2).
- Gallbladder disease (4, 5.5).
- Known hypersensitivity to fenofibrate (4).
- Nursing mothers (4, 8.2).

5 WARNINGS AND PRECAUTIONS

- Hepatotoxicity: Serious drug-induced liver injury, including liver transplantation and death, has been reported with TRICOR. Monitor patient’s liver function, including serum ALT, AST, and total bilirubin, at baseline and periodically for the duration of therapy. Discontinue if signs or symptoms of liver injury develop or if elevated enzyme levels persist (5.2).
- Myopathy and rhabdomyolysis: Have been reported in patients taking fenofibrate. Risks are increased during co-administration with a statin (with a significantly higher rate observed for gemfibrozil), particularly in elderly patients and patients with diabetes, renal failure, or hypothyroidism (5.3).
- Serum creatinine: TRICOR can reversibly increase serum creatinine levels (5.4). Monitor renal function periodically in patients with renal impairment (8.6).
- Cholelithiasis: TRICOR increases cholesterol excretion into the bile, leading to risk of cholelithiasis. If cholelithiasis is suspected, gallbladder studies are indicated (5.5).
- Coumarin anticoagulants: Use caution in concomitant treatment with oral coumarin anticoagulants. Adjust the dosage of coumarin anticoagulant to maintain the prothrombin time/INR at the desired level to prevent bleeding complications (5.6).
- Hypersensitivity Reactions: Acute hypersensitivity reactions, including anaphylaxis and angioedema, and delayed hypersensitivity reactions, including severe cutaneous adverse drug reactions have been reported postmarketing. Some cases were life-threatening and required emergency treatment. Discontinue fenofibrate and treat patients appropriately if reactions occur (5.9).

6 ADVERSE REACTIONS

Adverse reactions > 2% and at least 1% greater than placebo: Abnormal liver tests, increased AST, increased ALT, increased CPK, and rhinitis (6).

To report SUSPECTED ADVERSE REACTIONS, contact AbbVie Inc. at 1-800-633-9110 or FDA at 1-800-FDA-1088 or www.fda.gov/medwatch.

7 DRUG INTERACTIONS

- Coumarin anticoagulants: (7.1).
- Immunosuppressants: (7.2).
- Bile acid resins: (7.3).

8 USE IN SPECIFIC POPULATIONS

- Geriatric Use: Determine dose selection based on renal function (8.5).
- Renal Impairment: Avoid use in severe renal impairment patients. Dose reduction is required in mild to moderate renal impairment patients (8.6).

FULL PRESCRIBING INFORMATION

1 INDICATIONS AND USAGE

1.1 Primary Hypercholesterolemia or Mixed Dyslipidemia

TRICOR is indicated as adjunctive therapy to diet to reduce elevated low-density lipoprotein cholesterol (LDL-C), total cholesterol (Total-C), Triglycerides and apolipoprotein B (Apo B), and to increase high-density lipoprotein cholesterol (HDL-C) in adult patients with primary hypercholesterolemia or mixed dyslipidemia.

1.2 Severe Hypertriglyceridemia

TRICOR is also indicated as adjunctive therapy to diet for treatment of adult patients with severe hypertriglyceridemia. Improving glycemic control in diabetic patients showing fasting chylomicronemia will usually obviate the need for pharmacologic intervention.

Markedly elevated levels of serum triglycerides (e.g. > 2,000 mg/dL) may increase the risk of developing pancreatitis. The effect of fenofibrate therapy on reducing this risk has not been adequately studied.

1.3 Important Limitations of Use

Fenofibrate at a dose equivalent to 145 mg of TRICOR was not shown to reduce coronary heart disease morbidity and mortality in a large, randomized controlled trial of patients with type 2 diabetes mellitus [see Warnings and Precautions (5.1)].

2 DOSAGE AND ADMINISTRATION

2.1 General Considerations

Patients should be placed on an appropriate lipid-lowering diet before receiving TRICOR, and should continue this diet during treatment with TRICOR. TRICOR tablets can be given without regard to meals.

The initial treatment for dyslipidemia is dietary therapy specific for the type of lipoprotein abnormality. Excess body weight and excess alcoholic intake may be important factors in hypertriglyceridemia and should be addressed prior to any drug therapy. Physical exercise can be an important ancillary measure. Diseases contributory to hyperlipidemia, such as hypothyroidism or diabetes mellitus should be looked for and adequately treated. Estrogen therapy, thiazide diuretics and beta-blockers, are sometimes associated with massive rises in plasma triglycerides, especially in subjects with familial hypertriglyceridemia. In such cases, discontinuation of the specific etiologic agent may obviate the need for specific drug therapy of hypertriglyceridemia.

Lipid levels should be monitored periodically and consideration should be given to reducing the dosage of TRICOR if lipid levels fall significantly below the targeted range.

Therapy should be withdrawn in patients who do not have an adequate response after two months of treatment with the maximum recommended dose of 145 mg once daily.

2.2 Primary Hypercholesterolemia or Mixed Dyslipidemia

The initial dose of TRICOR is 145 mg once daily.

2.3 Severe Hypertriglyceridemia

The initial dose is 48 to 145 mg per day. Dosage should be individualized according to patient response, and should be adjusted if necessary following repeat lipid determinations at 4 to 8 week intervals. The maximum dose is 145 mg once daily.

2.4 Impaired Renal Function

Treatment with TRICOR should be initiated at a dose of 48 mg per day in patients having mild to moderately impaired renal function, and increased only after evaluation of the effects on renal function and lipid levels at this dose. The use of TRICOR should be avoided in patients with severe renal impairment [see Use in Specific Populations (8.6) and Clinical Pharmacology (12.3)].

2.5 Geriatric Patients

Dose selection for the elderly should be made on the basis of renal function [see Use in Specific Populations (8.5)].

3 DOSAGE FORMS AND STRENGTHS

- 48 mg yellow tablets, imprinted with the code identification letters “FI”.
- 48 mg yellow tablets, imprinted with the “a” logo and code identification letters “FI”.
- 145 mg white tablets, imprinted with the code identification letters “FO”.
- 145 mg white tablets, imprinted with the “a” logo and code identification letters “FO”.

4 CONTRAINDICATIONS

TRICOR is contraindicated in:

- patients with severe renal impairment, including those receiving dialysis [see Clinical Pharmacology (12.3)].
- patients with active liver disease, including those with primary biliary cirrhosis and unexplained persistent liver function abnormalities [see Warnings and Precautions (5.2)].
- patients with preexisting gallbladder disease [see Warnings and Precautions (5.5)].
- nursing mothers [see Use in Specific Populations (8.2)].
- patients with known hypersensitivity to fenofibrate or fenofibric acid [see Warnings and Precautions (5.9)].

5 WARNINGS AND PRECAUTIONS

5.1 Mortality and Coronary Heart Disease Morbidity

The effect of TRICOR on coronary heart disease morbidity and mortality and non-cardiovascular mortality has not been established.

The Action to Control Cardiovascular Risk in Diabetes Lipid (ACCORD Lipid) trial was a randomized placebo-controlled study of 5518 patients with type 2 diabetes mellitus on background statin therapy treated with fenofibrate. The mean duration of follow-up was 4.7 years. Fenofibrate plus statin combination therapy showed a non-significant 8% relative risk reduction in the primary outcome of major adverse cardiovascular events (MACE), a composite of non-fatal myocardial infarction, non-fatal stroke, and cardiovascular disease death (hazard ratio [HR] 0.92, 95% CI 0.79-1.08) (p=0.32) as compared to statin monotherapy. In a gender subgroup analysis, the hazard ratio for MACE in men receiving combination therapy versus statin monotherapy was 0.82 (95% CI 0.69-0.99), and the hazard ratio for MACE in women receiving combination therapy versus statin monotherapy was 1.38 (95% CI 0.98-1.94) (interaction p=0.01). The clinical significance of this subgroup finding is unclear.

The Fenofibrate Intervention and Event Lowering in Diabetes (FIELD) study was a 5-year randomized, placebo-controlled study of 9795 patients with type 2 diabetes mellitus treated with fenofibrate. Fenofibrate demonstrated a non-significant 11% relative reduction in the primary outcome of coronary heart disease events (hazard ratio [HR] 0.89, 95% CI 0.75-1.05, p=0.16) and a significant 11% reduction in the secondary outcome of total cardiovascular disease events (HR 0.89 [0.80-0.99], p=0.04). There was a non-significant 11% (HR 1.11 [0.95, 1.29], p=0.18) and 19% (HR 1.19 [0.90, 1.57], p=0.22) increase in total and coronary heart disease mortality, respectively, with fenofibrate as compared to placebo.

Because of chemical, pharmacological, and clinical similarities between TRICOR (fenofibrate tablets), clofibrate, and gemfibrozil, the adverse findings in 4 large randomized, placebo-controlled clinical studies with these other fibrate drugs may also apply to TRICOR.

In the Coronary Drug Project, a large study of post myocardial infarction of patients treated for 5 years with clofibrate, there was no difference in mortality seen between the clofibrate group and the placebo group. There was however, a difference in the rate of cholelithiasis and cholecystitis requiring surgery between the two groups (3.0% vs. 1.8%).

In a study conducted by the World Health Organization (WHO), 5000 subjects without known coronary artery disease were treated with placebo or clofibrate for 5 years and followed for an additional one year. There was a statistically significant, higher age − adjusted all-cause mortality in the clofibrate group compared with the placebo group (5.70% vs. 3.96%, p = < 0.01). Excess mortality was due to a 33% increase in non-cardiovascular causes, including malignancy, post-cholecystectomy complications, and pancreatitis. This appeared to confirm the higher risk of gallbladder disease seen in clofibrate-treated patients studied in the Coronary Drug Project.

The Helsinki Heart Study was a large (n=4081) study of middle-aged men without a history of coronary artery disease. Subjects received either placebo or gemfibrozil for 5 years, with a 3.5 year open extension afterward. Total mortality was numerically higher in the gemfibrozil randomization group but did not achieve statistical significance (p = 0.19, 95% confidence interval for relative risk G:P = .91-1.64). Although cancer deaths trended higher in the gemfibrozil group (p = 0.11), cancers (excluding basal cell carcinoma) were diagnosed with equal frequency in both study groups. Due to the limited size of the study, the relative risk of death from any cause was not shown to be different than that seen in the 9 year follow-up data from World Health Organization study (RR=1.29).

A secondary prevention component of the Helsinki Heart Study enrolled middle-aged men excluded from the primary prevention study because of known or suspected coronary heart disease. Subjects received gemfibrozil or placebo for 5 years. Although cardiac deaths trended higher in the gemfibrozil group, this was not statistically significant (hazard ratio 2.2, 95% confidence interval: 0.94-5.05). The rate of gallbladder surgery was not statistically significant between study groups, but did trend higher in the gemfibrozil group, (1.9% vs. 0.3%, p = 0.07).

5.2 Hepatotoxicity

Serious drug-induced liver injury (DILI), including liver transplantation and death, have been reported postmarketing with TRICOR. DILI has been reported within the first few weeks of treatment or after several months of therapy and in some cases has reversed with discontinuation of TRICOR treatment. Patients with DILI have experienced signs and symptoms including dark urine, abnormal stool, jaundice, malaise, abdominal pain, myalgia, weight loss, pruritus, and nausea. Many patients had concurrent elevations of total bilirubin, serum alanine transaminase (ALT), and aspartate transaminase (AST). DILI has been characterized as hepatocellular, chronic active, and cholestatic hepatitis, and cirrhosis has occurred in association with chronic active hepatitis.

In clinical trials, fenofibrate at doses equivalent to 96 mg to 145 mg TRICOR daily has been associated with increases in serum AST or ALT. The incidence of increases in transaminases may be dose related [see Adverse Reactions (6.1)].

TRICOR is contraindicated in patients with active liver disease, including those with primary biliary cirrhosis and unexplained persistent liver function abnormalities [see Contraindications (4)]. Monitor patient’s liver function, including serum ALT, AST, and total bilirubin, at baseline and periodically for the duration of therapy with TRICOR. Discontinue TRICOR if signs or symptoms of liver injury develop or if elevated enzyme levels persist (ALT or AST > 3 times the upper limit of normal, or if accompanied by elevation of bilirubin). Do not restart TRICOR in these patients if there is no alternative explanation for the liver injury.

5.3 Myopathy and Rhabdomyolysis

Fibrates increase the risk for myopathy and have been associated with rhabdomyolysis. The risk for serious muscle toxicity appears to be increased in elderly patients and in patients with diabetes, renal insufficiency, or hypothyroidism.

Myopathy should be considered in any patient with diffuse myalgias, muscle tenderness or weakness, and/or marked elevations of creatine phosphokinase (CPK) levels.

Patients should be advised to report promptly unexplained muscle pain, tenderness or weakness, particularly if accompanied by malaise or fever. CPK levels should be assessed in patients reporting these symptoms, and TRICOR therapy should be discontinued if markedly elevated CPK levels occur or myopathy/myositis is suspected or diagnosed.

Data from observational studies indicate that the risk for rhabdomyolysis is increased when fibrates, in particular gemfibrozil, are co-administered with a statin. The combination should be avoided unless the benefit of further alterations in lipid levels is likely to outweigh the increased risk of this drug combination [see Clinical Pharmacology (12.3)].

Cases of myopathy, including rhabdomyolysis, have been reported with fenofibrates co-administered with colchicine, and caution should be exercised when prescribing fenofibrate with colchicine [see Drug Interactions (7.4)].

5.4 Serum Creatinine

Elevations in serum creatinine have been reported in patients on fenofibrate. These elevations tend to return to baseline following discontinuation of fenofibrate. The clinical significance of these observations is unknown. Monitor renal function in patients with renal impairment taking TRICOR. Renal monitoring should also be considered for patients taking TRICOR at risk for renal insufficiency such as the elderly and patients with diabetes.

5.5 Cholelithiasis

Fenofibrate, like clofibrate and gemfibrozil, may increase cholesterol excretion into the bile, leading to cholelithiasis. If cholelithiasis is suspected, gallbladder studies are indicated. TRICOR therapy should be discontinued if gallstones are found.

5.6 Coumarin Anticoagulants

Caution should be exercised when coumarin anticoagulants are given in conjunction with TRICOR because of the potentiation of coumarin-type anticoagulant effects in prolonging the Prothrombin Time/International Normalized Ratio (PT/INR). To prevent bleeding complications, frequent monitoring of PT/INR and dose adjustment of the anticoagulant are recommended until PT/INR has stabilized [see Drug Interactions (7.1)].

5.7 Pancreatitis

Pancreatitis has been reported in patients taking fenofibrate, gemfibrozil, and clofibrate. This occurrence may represent a failure of efficacy in patients with severe hypertriglyceridemia, a direct drug effect, or a secondary phenomenon mediated through biliary tract stone or sludge formation with obstruction of the common bile duct.

5.8 Hematologic Changes

Mild to moderate hemoglobin, hematocrit, and white blood cell decreases have been observed in patients following initiation of fenofibrate therapy. However, these levels stabilize during long-term administration. Thrombocytopenia and agranulocytosis have been reported in individuals treated with fenofibrate. Periodic monitoring of red and white blood cell counts are recommended during the first 12 months of TRICOR administration.

5.9 Hypersensitivity Reactions

Acute Hypersensitivity

Anaphylaxis and angioedema have been reported postmarketing with fenofibrate. In some cases, reactions were life-threatening and required emergency treatment. If a patient develops signs or symptoms of an acute hypersensitivity reaction, advise them to seek immediate medical attention and discontinue fenofibrate.

Delayed Hypersensitivity

Severe cutaneous adverse drug reactions (SCAR), including Stevens-Johnson syndrome, toxic epidermal necrolysis, and Drug Reaction with Eosinophilia and Systemic Symptoms (DRESS), have been reported postmarketing, occurring days to weeks after initiation of fenofibrate. The cases of DRESS were associated with cutaneous reactions (such as rash or exfoliative dermatitis) and a combination of eosinophilia, fever, systemic organ involvement (renal, hepatic, or respiratory). Discontinue fenofibrate and treat patients appropriately if SCAR is suspected.

5.10 Venothromboembolic Disease

In the FIELD trial, pulmonary embolus (PE) and deep vein thrombosis (DVT) were observed at higher rates in the fenofibrate- than the placebo-treated group. Of 9,795 patients enrolled in FIELD, there were 4,900 in the placebo group and 4,895 in the fenofibrate group. For DVT, there were 48 events (1%) in the placebo group and 67 (1%) in the fenofibrate group (p = 0.074); and for PE, there were 32 (0.7%) events in the placebo group and 53 (1%) in the fenofibrate group (p = 0.022).

In the Coronary Drug Project, a higher proportion of the clofibrate group experienced definite or suspected fatal or nonfatal pulmonary embolism or thrombophlebitis than the placebo group (5.2% vs. 3.3% at five years; p < 0.01).

5.11 Paradoxical Decreases in HDL Cholesterol Levels

There have been postmarketing and clinical trial reports of severe decreases in HDL cholesterol levels (as low as 2 mg/dL) occurring in diabetic and non-diabetic patients initiated on fibrate therapy. The decrease in HDL-C is mirrored by a decrease in apolipoprotein A1. This decrease has been reported to occur within 2 weeks to years after initiation of fibrate therapy. The HDL-C levels remain depressed until fibrate therapy has been withdrawn; the response to withdrawal of fibrate therapy is rapid and sustained. The clinical significance of this decrease in HDL-C is unknown. It is recommended that HDL-C levels be checked within the first few months after initiation of fibrate therapy. If a severely depressed HDL-C level is detected, fibrate therapy should be withdrawn, and the HDL-C level monitored until it has returned to baseline, and fibrate therapy should not be re-initiated.

6 ADVERSE REACTIONS

The following serious adverse reactions are described below and elsewhere in the labeling:

- Mortality and coronary heart disease morbidity [see Warnings and Precautions (5.1)]
- Hepatoxicity [see Warnings and Precautions (5.2)]
- Pancreatitis [see Warnings and Precautions (5.7)]
- Hypersensitivity reactions [see Warnings and Precautions (5.9)]
- Venothromboembolic disease [see Warnings and Precautions (5.10)]

6.1 Clinical Trials Experience

Because clinical studies are conducted under widely varying conditions, adverse reaction rates observed in the clinical studies of a drug cannot be directly compared to rates in the clinical studies of another drug and may not reflect the rates observed in practice.

Adverse events reported by 2% or more of patients treated with fenofibrate (and greater than placebo) during the double-blind, placebo-controlled trials, regardless of causality, are listed in Table 1 below. Adverse events led to discontinuation of treatment in 5.0% of patients treated with fenofibrate and in 3.0% treated with placebo. Increases in liver function tests were the most frequent events, causing discontinuation of fenofibrate treatment in 1.6% of patients in double-blind trials.

Table 1. Adverse Reactions Reported by 2% or More of Patients Treated with Fenofibrate and Greater than Placebo During the Double-Blind, Placebo-Controlled Trials
BODY SYSTEM Adverse Reaction | Fenofibrate* (N=439) | Placebo (N=365)
BODY AS A WHOLE
Abdominal Pain | 4.6% | 4.4%
Back Pain | 3.4% | 2.5%
Headache | 3.2% | 2.7%
DIGESTIVE
Nausea | 2.3% | 1.9%
Constipation | 2.1% | 1.4%
METABOLIC AND NUTRITIONAL DISORDERS
Abnormal Liver Function Tests | 7.5%** | 1.4%
Increased ALT | 3.0% | 1.6%
Increased CPK | 3.0% | 1.4%
Increased AST | 3.4%** | 0.5%
RESPIRATORY
Respiratory Disorder | 6.2% | 5.5%
Rhinitis | 2.3% | 1.1%
* Dosage equivalent to 145 mg TRICOR.
** Significantly different from Placebo.

Urticaria was seen in 1.1% vs. 0%, and rash in 1.4% vs. 0.8% of fenofibrate and placebo patients respectively in controlled trials.

Increases in Liver Enzymes

In a pooled analysis of 10 placebo-controlled trials, increases to > 3 times the upper limit of normal in ALT occurred in 5.3% of patients taking fenofibrate at doses equivalent to 96 mg to 145 mg TRICOR daily versus 1.1% of patients treated with placebo [see Warnings and Precautions (5.2)]. In an 8-week study, the incidence of ALT or AST elevations ≥ 3 times the upper limit of normal was 13% in patients receiving dosages equivalent to 96 mg to 145 mg TRICOR daily and was 0% in those receiving dosages equivalent to 48 mg or less TRICOR daily or placebo.

6.2 Postmarketing Experience

The following adverse reactions have been identified during postapproval use of fenofibrate. Because these reactions are reported voluntarily from a population of uncertain size, it is not always possible to reliably estimate their frequency or establish a causal relationship to drug exposure: myalgia, rhabdomyolysis, pancreatitis, acute renal failure, muscle spasm, hepatitis, cirrhosis, increased total bilirubin, anemia, arthralgia, decreases in hemoglobin, decreases in hematocrit, white blood cell decreases, asthenia, severely depressed HDL-cholesterol levels, and interstitial lung disease. Photosensitivity reactions have occurred days to months after initiation; in some of these cases, patients reported a prior photosensitivity reaction to ketoprofen.

7 DRUG INTERACTIONS

7.1 Coumarin Anticoagulants

Potentiation of coumarin-type anticoagulant effects has been observed with prolongation of the PT/INR.

Caution should be exercised when coumarin anticoagulants are given in conjunction with TRICOR. The dosage of the anticoagulants should be reduced to maintain the PT/INR at the desired level to prevent bleeding complications. Frequent PT/INR determinations are advisable until it has been definitely determined that the PT/INR has stabilized [see Warnings and Precautions (5.6)].

7.2 Immunosuppressants

Immunosuppressants such as cyclosporine and tacrolimus can produce nephrotoxicity with decreases in creatinine clearance and rises in serum creatinine, and because renal excretion is the primary elimination route of fibrate drugs including TRICOR, there is a risk that an interaction will lead to deterioration of renal function. The benefits and risks of using TRICOR (fenofibrate tablets) with immunosuppressants and other potentially nephrotoxic agents should be carefully considered, and the lowest effective dose employed and renal function monitored.

7.3 Bile Acid Binding Resins

Since bile acid binding resins may bind other drugs given concurrently, patients should take TRICOR at least 1 hour before or 4 to 6 hours after a bile acid binding resin to avoid impeding its absorption.

7.4 Colchicine

Cases of myopathy, including rhabdomyolysis, have been reported with fenofibrates co-administered with colchicine, and caution should be exercised when prescribing fenofibrate with colchicine.

8 USE IN SPECIFIC POPULATIONS

8.1 Pregnancy

Risk Summary

Limited available data with fenofibrate use in pregnant women are insufficient to determine a drug associated risk of major birth defects, miscarriage or adverse maternal or fetal outcomes. In animal reproduction studies, no evidence of embryo-fetal toxicity was observed with oral administration of fenofibrate in rats and rabbits during organogenesis at doses less than or equivalent to the maximum recommended clinical dose of 145 mg daily, based on body surface area (mg/m^2). Adverse reproductive outcomes occurred at higher doses in the presence of maternal toxicity (see Data). TRICOR should be used during pregnancy only if the potential benefit justifies the potential risk to the fetus.

The estimated background risk of major birth defects and miscarriage for the indicated population is unknown. In the U.S. general population, the estimated background risk of major birth defects and miscarriage in clinically recognized pregnancies is 2-4% and 15-20%, respectively.

Data

Animal Data

In pregnant rats given oral dietary doses of 14, 127, and 361 mg/kg/day from gestation day 6-15 during the period of organogenesis, no adverse developmental findings were observed at 14 mg/kg/day (less than the clinical exposure at the maximum recommended human dose [MRHD] of 300 mg fenofibrate daily, equivalent to 145 mg TRICOR daily, based on body surface area comparisons). Increased fetal skeletal malformations were observed at maternally toxic doses (361 mg/kg/day, corresponding to 12 times the clinical exposure at the MRHD) that significantly suppressed maternal body weight gain.

In pregnant rabbits given oral gavage doses of 15, 150, and 300 mg/kg/day from gestation day 6-18 during the period of organogenesis and allowed to deliver, no adverse developmental findings were observed at 15 mg/kg/day (a dose that approximates the clinical exposure at the MRHD, based on body surface area comparisons). Aborted litters were observed at maternally toxic doses (≥ 150 mg/kg/day, corresponding to ≥ 10 times the clinical exposure at the MRHD) that suppressed maternal body weight gain.

In pregnant rats given oral dietary doses of 15, 75, and 300 mg/kg/day from gestation day 15 through lactation day 21 (weaning), no adverse developmental effects were observed at 15 mg/kg/day (less than the clinical exposure at the MRHD, based on body surface area comparisons), despite maternal toxicity (decreased weight gain). Post-implantation loss was observed at ≥ 75 mg/kg/day (≥ 2 times the clinical exposure at the MRHD) in the presence of maternal toxicity (decreased weight gain). Decreased pup survival was noted at 300 mg/kg/day (10 times the clinical exposure at the MRHD), which was associated with decreased maternal body weight gain/maternal neglect.

8.2 Lactation

Risk Summary

There is no available information on the presence of fenofibrate in human milk, effects of the drug on the breastfed infant, or the effects on milk production. Fenofibrate is present in the milk of rats, and is therefore likely to be present in human milk. Because of the potential for serious adverse reactions in breastfed infants, such as disruption of infant lipid metabolism, women should not breastfeed during treatment with TRICOR and for 5 days after the final dose [see Contraindications (4)].

8.4 Pediatric Use

Safety and effectiveness have not been established in pediatric patients.

8.5 Geriatric Use

Fenofibric acid is known to be substantially excreted by the kidney, and the risk of adverse reactions to this drug may be greater in patients with impaired renal function. Fenofibric acid exposure is not influenced by age. Since elderly patients have a higher incidence of renal impairment, dose selection for the elderly should be made on the basis of renal function [see Dosage and Administration (2.5) and Clinical Pharmacology (12.3)]. Elderly patients with normal renal function should require no dose modifications. Consider monitoring renal function in elderly patients taking TRICOR.

8.6 Renal Impairment

The use of TRICOR should be avoided in patients who have severe renal impairment [see Contraindications (4)]. Dose reduction is required in patients with mild to moderate renal impairment [see Dosage and Administration (2.4) and Clinical Pharmacology (12.3)]. Monitoring renal function in patients with renal impairment is recommended.

8.7 Hepatic Impairment

The use of TRICOR has not been evaluated in subjects with hepatic impairment [see Contraindications (4) and Clinical Pharmacology (12.3)].

10 OVERDOSAGE

There is no specific treatment for overdose with TRICOR. General supportive care of the patient is indicated, including monitoring of vital signs and observation of clinical status, should an overdose occur. If indicated, elimination of unabsorbed drug should be achieved by emesis or gastric lavage; usual precautions should be observed to maintain the airway. Because fenofibric acid is highly bound to plasma proteins, hemodialysis should not be considered.

11 DESCRIPTION

TRICOR (fenofibrate tablets), is a lipid regulating agent available as tablets for oral administration. Each tablet contains 48 mg or 145 mg of fenofibrate. The chemical name for fenofibrate is 2-[4-(4-chlorobenzoyl) phenoxy]-2-methyl-propanoic acid, 1-methylethyl ester with the following structural formula:

The empirical formula is C20H21O4Cl and the molecular weight is 360.83; fenofibrate is insoluble in water. The melting point is 79-82°C. Fenofibrate is a white solid which is stable under ordinary conditions.

Inactive Ingredients

Each tablet contains hypromellose 2910 (3 cps), docusate sodium, sucrose, sodium lauryl sulfate, lactose monohydrate, silicified microcrystalline cellulose, crospovidone, and magnesium stearate.

In addition, individual tablets contain:

48 mg tablets

polyvinyl alcohol, titanium dioxide, talc, soybean lecithin, xanthan gum, D&C Yellow #10 aluminum lake, FD&C Yellow #6 /sunset yellow FCF aluminum lake, FD&C Blue #2 /indigo carmine aluminum lake.

145 mg tablets

polyvinyl alcohol, titanium dioxide, talc, soybean lecithin, xanthan gum.

12 CLINICAL PHARMACOLOGY

12.1 Mechanism of Action

The active moiety of TRICOR is fenofibric acid. The pharmacological effects of fenofibric acid in both animals and humans have been extensively studied through oral administration of fenofibrate.

The lipid-modifying effects of fenofibric acid seen in clinical practice have been explained in vivo in transgenic mice and in vitro in human hepatocyte cultures by the activation of peroxisome proliferator activated receptor α (PPARα). Through this mechanism, fenofibrate increases lipolysis and elimination of triglyceride-rich particles from plasma by activating lipoprotein lipase and reducing production of apoprotein C-III (an inhibitor of lipoprotein lipase activity).

The resulting decrease in TG produces an alteration in the size and composition of LDL from small, dense particles (which are thought to be atherogenic due to their susceptibility to oxidation), to large buoyant particles. These larger particles have a greater affinity for cholesterol receptors and are catabolized rapidly. Activation of PPARα also induces an increase in the synthesis of apolipoproteins A-I, A-II and HDL-cholesterol.

Fenofibrate also reduces serum uric acid levels in hyperuricemic and normal individuals by increasing the urinary excretion of uric acid.

12.2 Pharmacodynamics

A variety of clinical studies have demonstrated that elevated levels of total-C, LDL-C, and apo B, an LDL membrane complex, are associated with human atherosclerosis. Similarly, decreased levels of HDL-C and its transport complex, apolipoprotein A (apo AI and apo AII) are associated with the development of atherosclerosis. Epidemiologic investigations have established that cardiovascular morbidity and mortality vary directly with the level of total-C, LDL-C, and TG, and inversely with the level of HDL-C. The independent effect of raising HDL-C or lowering triglycerides (TG) on the risk of cardiovascular morbidity and mortality has not been determined.

Fenofibric acid, the active metabolite of fenofibrate, produces reductions in total cholesterol, LDL cholesterol, apolipoprotein B, total triglycerides and triglyceride rich lipoprotein (VLDL) in treated patients. In addition, treatment with fenofibrate results in increases in high density lipoprotein (HDL) and apolipoproteins apoAI and apoAII.

12.3 Pharmacokinetics

Plasma concentrations of fenofibric acid after administration of three 48 mg or one 145 mg tablets are equivalent under fed conditions to one 200 mg micronized fenofibrate capsule.

Fenofibrate is a pro-drug of the active chemical moiety fenofibric acid. Fenofibrate is converted by ester hydrolysis in the body to fenofibric acid which is the active constituent measurable in the circulation.

Absorption

The absolute bioavailability of fenofibrate cannot be determined as the compound is virtually insoluble in aqueous media suitable for injection. However, fenofibrate is well absorbed from the gastrointestinal tract. Following oral administration in healthy volunteers, approximately 60% of a single dose of radiolabelled fenofibrate appeared in urine, primarily as fenofibric acid and its glucuronate conjugate, and 25% was excreted in the feces. Peak plasma levels of fenofibric acid occur within 6 to 8 hours after administration.

Exposure to fenofibric acid in plasma, as measured by Cmax and AUC, is not significantly different when a single 145 mg dose of fenofibrate is administered under fasting or nonfasting conditions.

Distribution

Upon multiple dosing of fenofibrate, fenofibric acid steady state is achieved within 9 days. Plasma concentrations of fenofibric acid at steady state are approximately double of those following a single dose. Serum protein binding was approximately 99% in normal and hyperlipidemic subjects.

Metabolism

Following oral administration, fenofibrate is rapidly hydrolyzed by esterases to the active metabolite, fenofibric acid; no unchanged fenofibrate is detected in plasma.

Fenofibric acid is primarily conjugated with glucuronic acid and then excreted in urine. A small amount of fenofibric acid is reduced at the carbonyl moiety to a benzhydrol metabolite which is, in turn, conjugated with glucuronic acid and excreted in urine.

In vivo metabolism data indicate that neither fenofibrate nor fenofibric acid undergo oxidative metabolism (e.g., cytochrome P450) to a significant extent.

Elimination

After absorption, fenofibrate is mainly excreted in the urine in the form of metabolites, primarily fenofibric acid and fenofibric acid glucuronide. After administration of radiolabelled fenofibrate, approximately 60% of the dose appeared in the urine and 25% was excreted in the feces.

Fenofibric acid is eliminated with a half-life of 20 hours, allowing once daily dosing.

Special Populations

Geriatrics

In elderly volunteers 77 to 87 years of age, the oral clearance of fenofibric acid following a single oral dose of fenofibrate was 1.2 L/h, which compares to 1.1 L/h in young adults. This indicates that a similar dosage regimen can be used in elderly with normal renal function, without increasing accumulation of the drug or metabolites [see Dosage and Administration (2.5) and Use in Specific Populations (8.5)].

Pediatrics

The pharmacokinetics of TRICOR has not been studied in pediatric populations.

Gender

No pharmacokinetic difference between males and females has been observed for fenofibrate.

Race

The influence of race on the pharmacokinetics of fenofibrate has not been studied, however fenofibrate is not metabolized by enzymes known for exhibiting inter-ethnic variability.

Renal Impairment

The pharmacokinetics of fenofibric acid was examined in patients with mild, moderate, and severe renal impairment. Patients with severe renal impairment (estimated glomerular filtration rate [eGFR] < 30 mL/min/1.73m^2) showed 2.7-fold increase in exposure for fenofibric acid and increased accumulation of fenofibric acid during chronic dosing compared to that of healthy subjects. Patients with mild to moderate renal impairment (eGFR 30-59 mL/min/1.73m^2) had similar exposure but an increase in the half-life for fenofibric acid compared to that of healthy subjects. Based on these findings, the use of TRICOR should be avoided in patients who have severe renal impairment and dose reduction is required in patients having mild to moderate renal impairment [see Dosage and Administration (2.4)].

Hepatic Impairment

No pharmacokinetic studies have been conducted in patients with hepatic impairment.

Drug-drug Interactions

In vitro studies using human liver microsomes indicate that fenofibrate and fenofibric acid are not inhibitors of cytochrome (CYP) P450 isoforms CYP3A4, CYP2D6, CYP2E1, or CYP1A2. They are weak inhibitors of CYP2C8, CYP2C19 and CYP2A6, and mild-to-moderate inhibitors of CYP2C9 at therapeutic concentrations.

Table 2 describes the effects of co-administered drugs on fenofibric acid systemic exposure. Table 3 describes the effects of co-administered fenofibrate or fenofibric acid on other drugs.

Table 2. Effects of Co-Administered Drugs on Fenofibric Acid Systemic Exposure from Fenofibrate Administration
Co- Administered Drug | Dosage Regimen of Co-Administered Drug | Dosage Regimen of Fenofibrate | Changes in Fenofibric Acid Exposure
 |  |  | AUC | Cmax
Lipid-lowering agents
Atorvastatin | 20 mg once daily for 10 days | Fenofibrate 160 mg^1 once daily for 10 days | ↓2% | ↓4%
Pravastatin | 40 mg as a single dose | Fenofibrate 3 x 67 mg^2 as a single dose | ↓1% | ↓2%
Fluvastatin | 40 mg as a single dose | Fenofibrate 160 mg^1 as a single dose | ↓2% | ↓10%
Anti-diabetic agents
Glimepiride | 1 mg as a single dose | Fenofibrate 145 mg^1 once daily for 10 days | ↑1% | ↓1%
Metformin | 850 mg three times daily for 10 days | Fenofibrate 54 mg^1 three times daily for 10 days | ↓9% | ↓6%
Rosiglitazone | 8 mg once daily for 5 days | Fenofibrate 145 mg^1 once daily for 14 days | ↑10% | ↑3%
^1 TriCor (fenofibrate) oral tablet
^2 TriCor (fenofibrate) oral micronized capsule

Table 3. Effects of Fenofibrate Co-Administration on Systemic Exposure of Other Drugs
Dosage Regimen of Fenofibrate | Dosage Regimen of Co- Administered Drug | Change in Co-Administered Drug Exposure
 |  | Analyte | AUC | Cmax
Lipid-lowering agents
Fenofibrate 160 mg^1 once daily for 10 days | Atorvastatin, 20 mg once daily for 10 days | Atorvastatin | ↓17% | 0%
Fenofibrate 3 x 67 mg^2 as a single dose | Pravastatin, 40 mg as a single dose | Pravastatin | ↑13% | ↑13%
 |  | 3α-Hydroxyl-iso- pravastatin | ↑26% | ↑29%
Fenofibrate 160 mg^1 as a single dose | Fluvastatin, 40 mg as a single dose | (+)-3R, 5S- Fluvastatin | ↑15% | ↑16%
Anti-diabetic agents
Fenofibrate 145 mg^1 once daily for 10 days | Glimepiride, 1 mg as a single dose | Glimepiride | ↑35% | ↑18%
Fenofibrate 54 mg^1 three times daily for 10 days | Metformin, 850 mg three times daily for 10 days | Metformin | ↑3% | ↑6%
Fenofibrate 145 mg^1 once daily for 14 days | Rosiglitazone, 8 mg once daily for 5 days | Rosiglitazone | ↑6% | ↓1%
^1 TriCor (fenofibrate) oral tablet
^2 TriCor (fenofibrate) oral micronized capsule

13 NONCLINICAL TOXICOLOGY

13.1 Carcinogenesis and Mutagenesis and Impairment of Fertility

Two dietary carcinogenicity studies have been conducted in rats with fenofibrate. In the first 24-month study, Wistar rats were dosed with fenofibrate at 10, 45, and 200 mg/kg/day, approximately 0.3, 1, and 6 times the maximum recommended human dose (MRHD) of 300 mg fenofibrate daily, equivalent to 145 mg TRICOR daily, based on body surface area comparisons. At a dose of 200 mg/kg/day (at 6 times the MRHD), the incidence of liver carcinomas was significantly increased in both sexes. A statistically significant increase in pancreatic carcinomas was observed in males at 1 and 6 times the MRHD; an increase in pancreatic adenomas and benign testicular interstitial cell tumors was observed at 6 times the MRHD in males. In a second 24-month rat carcinogenicity study in a different strain of rats (Sprague-Dawley), doses of 10 and 60 mg/kg/day (0.3 and 2 times the MRHD) produced significant increases in the incidence of pancreatic acinar adenomas in both sexes and increases in testicular interstitial cell tumors in males at 2 times the MRHD.

A 117-week carcinogenicity study was conducted in rats comparing three drugs: fenofibrate 10 and 60 mg/kg/day (0.3 and 2 times the MRHD, based on body surface area comparisons), clofibrate (400 mg/kg/day; 2 times the human dose), and gemfibrozil (250 mg/kg/day; 2 times the human dose, based on mg/m^2 surface area). Fenofibrate increased pancreatic acinar adenomas in both sexes. Clofibrate increased hepatocellular carcinoma and pancreatic acinar adenomas in males and hepatic neoplastic nodules in females. Gemfibrozil increased hepatic neoplastic nodules in males and females, while all three drugs increased testicular interstitial cell tumors in males.

In a 21-month study in CF-1 mice, fenofibrate 10, 45, and 200 mg/kg/day (approximately 0.2, 1, and 3 times the MRHD, based on body surface area comparisons) significantly increased the liver carcinomas in both sexes at 3 times the MRHD. In a second 18-month study at 10, 60, and 200 mg/kg/day, fenofibrate significantly increased the liver carcinomas in male mice and liver adenomas in female mice at 3 times the MRHD.

Electron microscopy studies have demonstrated peroxisomal proliferation following fenofibrate administration to the rat. An adequate study to test for peroxisome proliferation in humans has not been done, but changes in peroxisome morphology and numbers have been observed in humans after treatment with other members of the fibrate class when liver biopsies were compared before and after treatment in the same individual.

Fenofibrate has been demonstrated to be devoid of mutagenic potential in the following tests: Ames, mouse lymphoma, chromosomal aberration and unscheduled DNA synthesis in primary rat hepatocytes.

In fertility studies rats were given oral dietary doses of fenofibrate, males received 61 days prior to mating and females 15 days prior to mating through weaning which resulted in no adverse effect on fertility at doses up to 300 mg/kg/day (10 times the MRHD, based on body surface area comparisons).

14 CLINICAL STUDIES

14.1 Primary Hypercholesterolemia (Heterozygous Familial and Nonfamilial) and Mixed Dyslipidemia

The effects of fenofibrate at a dose equivalent to 145 mg TRICOR (fenofibrate tablets) per day were assessed from four randomized, placebo-controlled, double-blind, parallel-group studies including patients with the following mean baseline lipid values: total-C 306.9 mg/dL; LDL-C 213.8 mg/dL; HDL-C 52.3 mg/dL; and triglycerides 191.0 mg/dL. TRICOR therapy lowered LDL-C, Total-C, and the LDL-C/HDL-C ratio. TRICOR therapy also lowered triglycerides and raised HDL-C (see Table 4).

Table 4. Mean Percent Change in Lipid Parameters at End of Treatment†
Treatment Group | Total-C | LDL-C | HDL-C | TG
Pooled Cohort
Mean baseline lipid values (n=646) | 306.9 mg/dL | 213.8 mg/dL | 52.3 mg/dL | 191.0 mg/dL
All FEN (n=361) | -18.7%* | -20.6%* | +11.0%* | -28.9%*
Placebo (n=285) | -0.4% | -2.2% | +0.7% | +7.7%
Baseline LDL-C > 160 mg/dL and TG < 150 mg/dL
Mean baseline lipid values (n=334) | 307.7 mg/dL | 227.7 mg/dL | 58.1 mg/dL | 101.7 mg/dL
All FEN (n=193) | -22.4%* | -31.4%* | +9.8%* | -23.5%*
Placebo (n=141) | +0.2% | -2.2% | +2.6% | +11.7%
Baseline LDL-C >160 mg/dL and TG ≥ 150 mg/dL
Mean baseline lipid values (n=242) | 312.8 mg/dL | 219.8 mg/dL | 46.7 mg/dL | 231.9 mg/dL
All FEN (n=126) | -16.8%* | -20.1%* | +14.6%* | -35.9%*
Placebo (n=116) | -3.0% | -6.6% | +2.3% | +0.9%
† Duration of study treatment was 3 to 6 months.
* p = < 0.05 vs. Placebo

In a subset of the subjects, measurements of apo B were conducted. TRICOR treatment significantly reduced apo B from baseline to endpoint as compared with placebo (-25.1% vs. 2.4%, p < 0.0001, n=213 and 143 respectively).

14.2 Severe Hypertriglyceridemia

The effects of fenofibrate on serum triglycerides were studied in two randomized, double-blind, placebo-controlled clinical trials of 147 hypertriglyceridemic patients. Patients were treated for eight weeks under protocols that differed only in that one entered patients with baseline TG levels of 500 to 1500 mg/dL, and the other TG levels of 350 to 500 mg/dL. In patients with hypertriglyceridemia and normal cholesterolemia with or without hyperchylomicronemia, treatment with fenofibrate at dosages equivalent to TRICOR 145 mg per day decreased primarily very low density lipoprotein (VLDL) triglycerides and VLDL cholesterol. Treatment of patients with elevated triglycerides often results in an increase of LDL-C (see Table 5).

Table 5. Effects of TRICOR in Patients With Severe Hypertriglyceridemia
Study 1 | Placebo |  |  |  | TRICOR
Baseline TG levels 350 to 499 mg/dL | N | Baseline (Mean) | Endpoint (Mean) | % Change (Mean) | N | Baseline (Mean) | Endpoint (Mean) | % Change (Mean)
Triglycerides | 28 | 449 | 450 | -0.5 | 27 | 432 | 223 | -46.2*
VLDL Triglycerides | 19 | 367 | 350 | 2.7 | 19 | 350 | 178 | -44.1*
Total Cholesterol | 28 | 255 | 261 | 2.8 | 27 | 252 | 227 | -9.1*
HDL Cholesterol | 28 | 35 | 36 | 4 | 27 | 34 | 40 | 19.6*
LDL Cholesterol | 28 | 120 | 129 | 12 | 27 | 128 | 137 | 14.5
VLDL Cholesterol | 27 | 99 | 99 | 5.8 | 27 | 92 | 46 | -44.7*
Study 2 | Placebo |  |  |  | TRICOR
Baseline TG levels 500 to 1500 mg/dL | N | Baseline (Mean) | Endpoint (Mean) | % Change (Mean) | N | Baseline (Mean) | Endpoint (Mean) | % Change (Mean)
Triglycerides | 44 | 710 | 750 | 7.2 | 48 | 726 | 308 | -54.5*
VLDL Triglycerides | 29 | 537 | 571 | 18.7 | 33 | 543 | 205 | -50.6*
Total Cholesterol | 44 | 272 | 271 | 0.4 | 48 | 261 | 223 | -13.8*
HDL Cholesterol | 44 | 27 | 28 | 5.0 | 48 | 30 | 36 | 22.9*
LDL Cholesterol | 42 | 100 | 90 | -4.2 | 45 | 103 | 131 | 45.0*
VLDL Cholesterol | 42 | 137 | 142 | 11.0 | 45 | 126 | 54 | -49.4*
* =p < 0.05 vs. Placebo

The effect of TRICOR on cardiovascular morbidity and mortality has not been determined.

16 HOW SUPPLIED/STORAGE AND HANDLING

Product: 50090-2899

NDC: 50090-2899-2 90 TABLET in a BOTTLE

17 PATIENT COUNSELING INFORMATION

Patients should be advised:

- of the potential benefits and risks of TRICOR.
- not to use TRICOR if there is a known hypersensitivity to fenofibrate or fenofibric acid.
- of medications that should not be taken in combination with TRICOR.
- that if they are taking coumarin anticoagulants, TRICOR may increase their anti-coagulant effect, and increased monitoring may be necessary.
- to continue to follow an appropriate lipid-modifying diet while taking TRICOR.
- to take TRICOR once daily, without regard to food, at the prescribed dose, swallowing each tablet whole.
- to return to their physician’s office for routine monitoring.
- to inform their physician of all medications, supplements, and herbal preparations they are taking and any change to their medical condition. Patients should also be advised to inform their physicians prescribing a new medication that they are taking TRICOR.
- to inform their physician of symptoms of liver injury (e.g., jaundice, abdominal pain, nausea, malaise, dark urine, abnormal stool, pruritus); any muscle pain, tenderness, or weakness; or any other new symptoms.
- not to breastfeed during treatment with TRICOR and for 5 days after the final dose.

Manufactured for AbbVie Inc., North Chicago, IL 60064, U.S.A.
by Fournier Laboratories Ireland Limited, Anngrove, Carrigtwohill Co. Cork, Ireland.

20067131 June, 2021